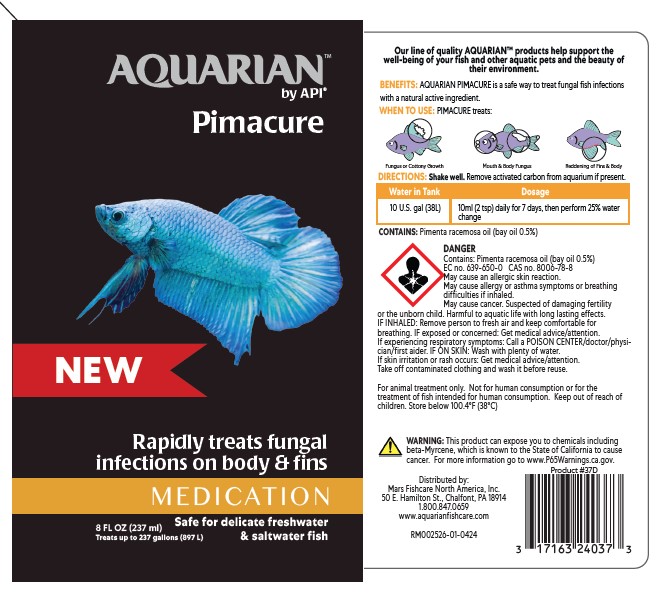 DRUG LABEL: AQUARIAN PIMACURE
NDC: 17163-240 | Form: LIQUID
Manufacturer: MARS FISHCARE NORTH AMERICA, INC.
Category: animal | Type: OTC ANIMAL DRUG LABEL
Date: 20240604

ACTIVE INGREDIENTS: BAY OIL (PIMENTA RACEMOSA) 1 g/100 mL

Drug Label

DESCRIPTION

Our line of quality AQUARIAN™ products help support the well-being of your fish and other aquatic pets and the beauty of thier environment.

BENEFITS: AQUARIAN PIMACURE is a safe way to treat fungal fish infections with a natural active ingredient.

INDICATIONS AND USAGE

WHEN TO USE: PIMAFIX treats:

Fungus or Cottony Growth

Mouth and Body Fungus

Reddening of Fins and Body

DIRECTIONS:

Shake well. Remove activated carbon from aquarium if present.

Water in Tank Dosage

10 U.S. gal (38L) 10 ml (2 tsp) daily for 7 days, then perform 25% water change

ACTIVE INGREDIENT

CONTAINS: Pimenta racemosa 0.5%

USER SAFETY WARNINGS

DANGER

Contains: Pimenta racemosa oil (bay oil 0.5%)

EC no. 639-650-0 CAS n. 8006-78-8

May cause an allergic skin reation.

May cause allergy or asthma symptoms or breathing difficulties if inhaled.

May cause cancer. Suspected of damaging fertility or the unborn child. Harmfuul to aquatic life with long lasting effects.

IF INHALED: Remove person to fresh air and keep comfortable for breathing. IF exposed or concerned: Get medical advice/attention. If experiencing respiratory symptoms: CALL a POISON CENTER/doctor/physician/first aider. IF ON SKIN: Wash with plenty of water. If skin irritation or rash occurs: Get medical advice/attention. Take off contaminated clothing and wash it before reuse.

For animal treatment only. Not for human consumption or for the treatment of fish intended for human consumption.

Keep out of reach of children. Store below 100.4°F (38°C)

Warning: This product can expose you to chemicals including beta-Myrcene, which is know to the State of California to cause cancer. For more information go to www.P65Warnings.ca.gov.

PACKAGE LABEL

AQUARIAN™

by API®

Pimacure

NEW

Rapidly treats fungal infections on body and fins

MEDICATION

Safe for delicate freshwater and saltwater fish

8 FL OZ (237)

Treats up to 237 gallons (897L)